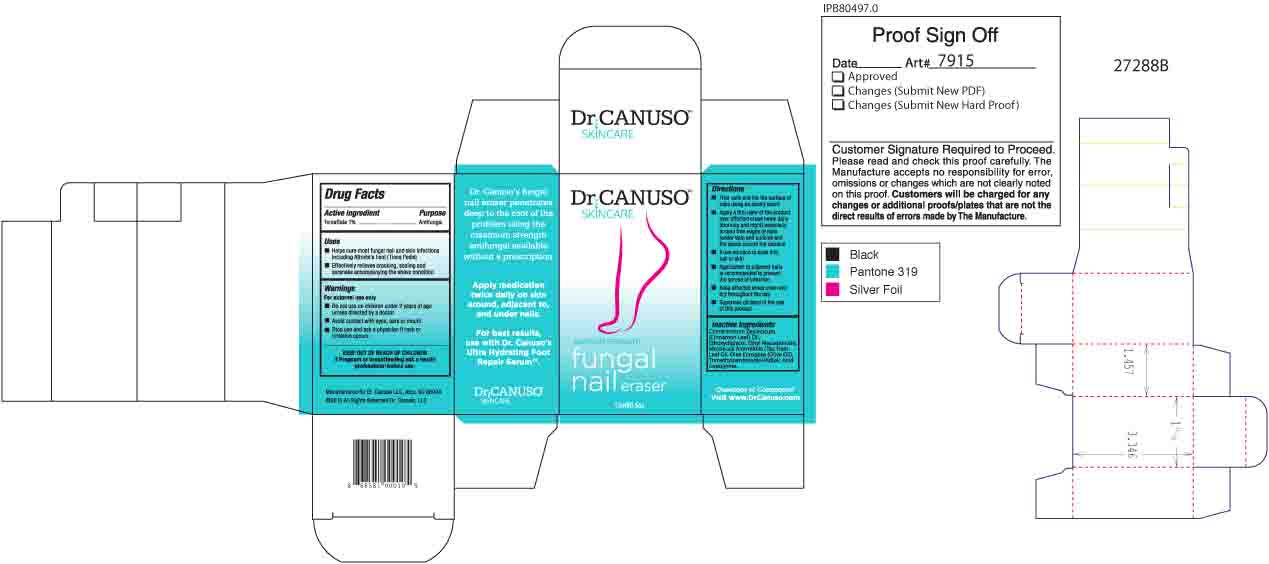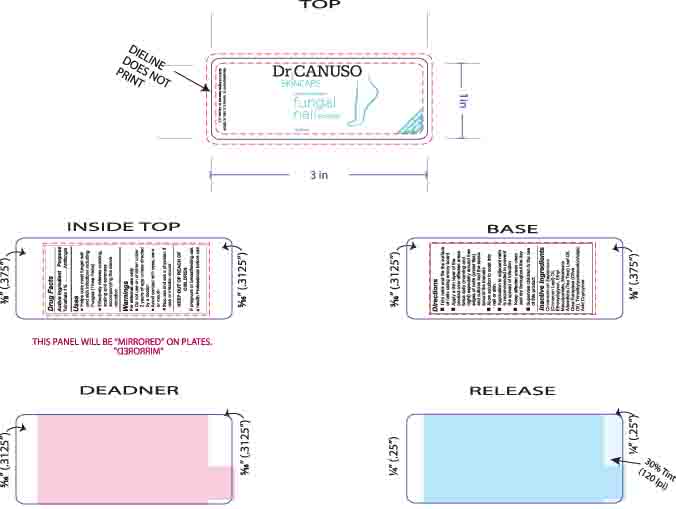 DRUG LABEL: Dr CANUSO fungal nail eraser
NDC: 76348-410 | Form: OIL
Manufacturer: Renu Laboratories, LLC
Category: otc | Type: HUMAN OTC DRUG LABEL
Date: 20250513

ACTIVE INGREDIENTS: TOLNAFTATE 0.3 g/28 g
INACTIVE INGREDIENTS: ETHYL MACADAMIATE; DIETHYLENE GLYCOL MONOETHYL ETHER; CINNAMON LEAF OIL; TEA TREE OIL; TRIMETHYLPENTANEDIOL/ADIPIC ACID/GLYCERIN CROSSPOLYMER (25000 MPA.S); ALKYL (C12-15) BENZOATE; OLIVE OIL

Dr. CANUSO Fungal Nail Eraser

Active Ingredient

Tolnaftate 1%

Purpose

Antifungal

Uses

- Helps cure most fungal nail and skin infections including Fungus (Tinea Pedis)
- Effectively relieves cracking, scaling and soreness accompanying the above conditon

Warnings

For external use only

- Do not use on children under 2 years of age unless directed by a doctor
- Avoid contact with eyes, ears or mouth
- Stop use and ask a physician if rash or irritation occurs

KEEP OUT OF REACH OF CHILDREN

PREGNANCY OR BREAST FEEDING

If pregnant or breastfeeding ask a health Professional before use

Directions

- Trim nails and file the surface of nails using an emory board
- Apply a thin layer of the product over affected areas twice daily (morning and night) especially around free edges of nails (under tips) and cuticles and the space around the toenails.
- Allow solution to soak into nail or skin
- Application to adjacent nails is recommended to prevent the spread of infection
- Keep affected areas clean and dry throughout the day
- Supervise children in the use of this product

Inactive Ingredients

Cinnamomum Zeylanicum (Cinnamon Leaf) Oil, Ethoxydiglycol, Ethyl Macadamiate, Melaleuca Alternifolia (Tea Tree) Leaf Oil, Olea Europaea (Olive Oil), Trimethylpentanediol/Adipic Acid Copolymer.

Questions or Comments?

Visit www.DrCanuso.com

Uses

- Helps cure most fungal nail and skin infections including Athlete's Foot (Tinea Pedis)
- Effectively relieves cracking, scaling and soreness accompanying the above condition